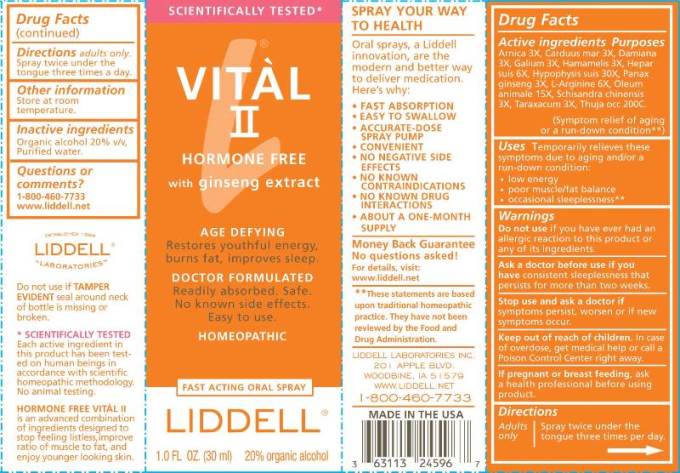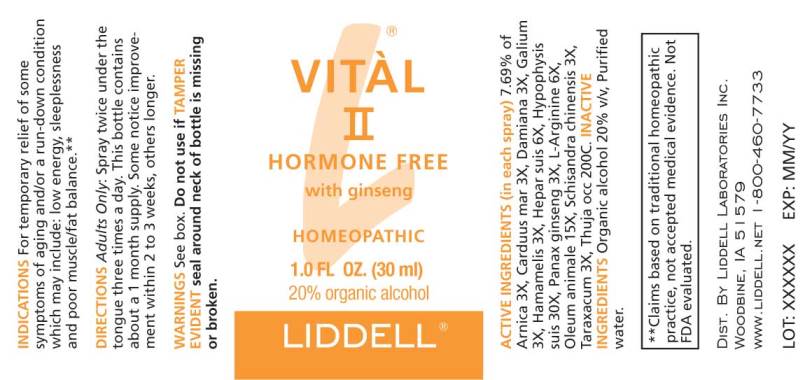 DRUG LABEL: VITAL
NDC: 50845-0257 | Form: SPRAY
Manufacturer: Liddell Laboratories, Inc.
Category: homeopathic | Type: HUMAN OTC DRUG LABEL
Date: 20240701

ACTIVE INGREDIENTS: ARNICA MONTANA WHOLE 3 [hp_X]/1 mL; MILK THISTLE 3 [hp_X]/1 mL; TURNERA DIFFUSA LEAFY TWIG 3 [hp_X]/1 mL; GALIUM APARINE WHOLE 3 [hp_X]/1 mL; HAMAMELIS VIRGINIANA ROOT BARK/STEM BARK 3 [hp_X]/1 mL; PORK LIVER 6 [hp_X]/1 mL; SUS SCROFA PITUITARY GLAND 30 [hp_X]/1 mL; ASIAN GINSENG 3 [hp_X]/1 mL; ARGININE 6 [hp_X]/1 mL; CERVUS ELAPHUS HORN OIL 15 [hp_X]/1 mL; SCHISANDRA CHINENSIS FRUIT 3 [hp_X]/1 mL; TARAXACUM OFFICINALE 3 [hp_X]/1 mL; THUJA OCCIDENTALIS LEAFY TWIG 200 [hp_C]/1 mL
INACTIVE INGREDIENTS: WATER; ALCOHOL

DRUG FACTS:

ACTIVE INGREDIENTS:

(in each spray) 7.69% of Arnica Montana 3X, Carduus Marianus 3X, Damiana 3X, Galium Aparine 3X, Hamamelis Virginiana 3X, Hepar Suis 6X, Hypophysis Suis 6X, Panax Ginseng 3X, L-Arginine 6X, Oleum Animale 15X, Schisandra Chinensis 3X, Taraxacum Officinale 3X, Thuja Occidentalis 200C.

USES:

Temporarily relieves these symptoms due to aging and/or a run-down condition:

• low energy

• poor muscle/fat balance

• occasional sleeplessness

WARNINGS:

Do not use if you have ever had an allergic reaction to this product or any of its ingredients.

Ask a doctor before use if you have consistent sleeplessness that persists for more than two weeks.

Stop use and ask a doctor if symptoms persist, worsen or if new symptoms occur.

Keep out of reach of children. In case of overdose, get medical help or call a Poison Control Center right away.

If pregnant or breast-feeding, ask a health professional before using product.

Do not use if TAMPER EVIDENT seal around neck of bottle is missing or broken.

Store at room temperature.

Keep out of reach of children. In case of overdose, get medical help or call a Poison Control Center right away.

DIRECTIONS:

Adults only.

Spray twice under the tongue three times a day.

USES:

Temporarily relieves these symptoms due to aging and/or a run-down condition:

• low energy

• poor muscle/fat balance

• occasional sleeplessness

INACTIVE INGREDIENTS:

Purified Water, Organic Ethanol 20%

QUESTIONS:

DISTRIBUTED BY:

Liddell Laboratories

201 Apple Blvd

Woodbine, IA 51579

www.liddell.net

1-800-460-7733

PACKAGE LABEL DISPLAY:

VITÀL

II

HORMONE FREE

with ginseng extract

AGE DEFYING

Restores youthful energy,

burns fat, improves sleep.

DOCTOR FORMULATED

Readily absorbed. Safe.

No known side effects.

Easy to use

HOMEOPATHIC

FAST ACTING ORAL SPRAY

LIDDELL

1.0 FL OZ (30 ml)